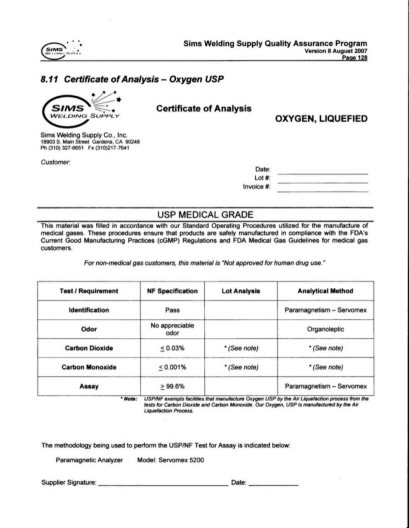 DRUG LABEL: OXYGEN
NDC: 55586-001 | Form: GAS
Manufacturer: Sims Welding Supply Co, Inc.
Category: prescription | Type: HUMAN PRESCRIPTION DRUG LABEL
Date: 20100101

ACTIVE INGREDIENTS: OXYGEN 99 L/100 L

OXYGEN CERTIFICATE OF ANALYSIS

SIMS WELDING SUPPLY QUALITY ASSURANCE PROGRAM VERSION 8 AUGUST 2007 PAGE 128

8.11 CERTIFICATE OF ANALYSIS - OXYGEN USP

CERTIFICATE OF ANALYSIS OXYGEN LIQUEFIED

CUSTOMER____ DATE______LOT#____________INVOICE#___________________

USP MEDICAL GRADE

TEST/REQUIREMENT NF SPECIFICATION LOT ANALYSIS ANALYTICAL METHOD

IDENTIFICATION PASS PARAMAGNETISM - SERVOMEX

ODOR NO APPRECIABLE ODOR ORGANOLEPTIC

CARBON DIOXIDE LESS THAN OR EQUAL TO 0.03% SEE NOTE SEE NOTE

CARBON MONOXIDE LESS THAN OR EQUAL TO 0.001% SEE NOTE SEE NOTE

ASSAY GREATER THAN OR EQUAL TO 99.6% PARAMAGNETISM - SERVOMEX

NOTE: USP/NF EXEMPTS FACILITIES THAT MANUFACTURE OXYGEN USP BY THE AIR LIQUEFACTION PROCESS FROM THE TESTS FOR CARBON DIOXIDE AND CARBON MONOXIDE. OUR OXYGEN USP IS MANUFACTURED BY THE AIR LIQUEFACTION PROCESS

THE METHODOLOGY BEING USED TO PERFORM THE USP/NF TEST FOR ASSAY IS INDICATED BELOW:

PARAMAGNETIC ANALYZER MODEL: SERVOMEX 5200

SUPPLIER SIGNATURE:_____________________________ DATE:___________________

WARNINGS AND PRECAUTIONS

THIS MATERIAL WAS FILLED IN ACCORDANCE WITH OUR STANDARD OPERATING PROCEDURES UTILIZED FOR THE MANUFACTURE OF MEDICAL GASES. THESE PROCEDURES ENSURE THAT PRODUCTS ARE SAFELY MANUFACTURED IN COMPLIANCE WITH THE FDA'S CURRENT GOOD MANUFACTURING PRACTICES (cGMP) REGULATIONS AND FDA MEDICAL GAS GUIDELINES FOR MEDICAL GAS CUSTOMERS. FOR NON-MEDICAL CUSTOMERS, THIS MATERIAL IS NOT APPROVED FOR HUMAN DRUG USE.